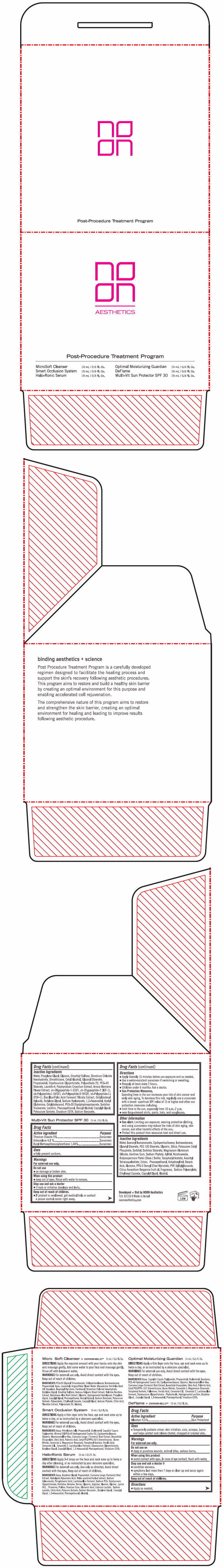 DRUG LABEL: NOON Post Procedure Program
NDC: 78863-2600 | Form: KIT | Route: TOPICAL
Manufacturer: Noon Aesthetics M.R. Ltd
Category: otc | Type: HUMAN OTC DRUG LABEL
Date: 20250114

ACTIVE INGREDIENTS: ALLANTOIN 5 mg/1 mL; TITANIUM DIOXIDE 90 mg/1 mL; OCTOCRYLENE 48 mg/1 mL; AVOBENZONE 14.4 mg/1 mL
INACTIVE INGREDIENTS: WATER; PROPYLENE GLYCOL; GLYCERIN; DIMETHYL SULFONE; STRONTIUM CHLORIDE HEXAHYDRATE; DIMETHICONE; CETYL ALCOHOL; GLYCERYL MONOSTEARATE; PROPANEDIOL; GLYCYRRHIZINATE DIPOTASSIUM; POLYSORBATE 20; LAURETH-4; ARNICA MONTANA FLOWER; OCTYLDODECYL XYLOSIDE; BUTYLENE GLYCOL; HYALURONATE SODIUM; 1,2-HEXANEDIOL; ACEGLUTAMIDE; OCTYLDODECANOL; PEG-30 DIPOLYHYDROXYSTEARATE (4000 MW); SORBITAN TRISTEARATE; PHENOXYETHANOL; BENZYL ALCOHOL; CAPRYLYL GLYCOL; POTASSIUM SORBATE; EDETATE DISODIUM ANHYDROUS; SODIUM BENZOATE; WATER; ISONONYL ISONONANOATE; CYCLOMETHICONE 5; ISOHEXADECANE; GLYCERYL MONOSTEARATE; PEG-100 STEARATE; GLYCERIN; SILICON DIOXIDE; POTASSIUM CETYL PHOSPHATE; SORBITOL; SORBITAN MONOSTEARATE; MAGNESIUM ALUMINUM SILICATE; XANTHAN GUM; PHYTATE SODIUM; XYLITOL; NIACINAMIDE; SHEA BUTTER; .ALPHA.-TOCOPHEROL ACETATE; ASCORBYL TETRAISOPALMITATE; ECTOINE; PHENOXYETHANOL; ANHYDROXYLITOL; STEARIC ACID; ALUMINUM OXIDE; PPG-3 BENZYL ETHER MYRISTATE; POVIDONE, UNSPECIFIED; XYLITYLGLUCOSIDE; ETHYLHEXYL COCOATE; CAPRYLYL GLYCOL; ALCOHOL

NOON Post Procedure Program

DeFlame + DERMSHIELD™

Drug Facts

Active Ingredient

Allantoin 0.5%

Purpose

Skin Protectant

Uses

- Temporarily protects minor: skin irritation, cuts, scrapes, burns and helps protect and relieve chafed, chapped or cracked skin.

Warnings

For external use only.

Do not use on

- deep or puncture wounds, animal bites, serious burns.

When using this product

- avoid contact with eyes. In case of eye contact, flush with water.

Stop use and ask a doctor if

- condition worsens.
- symptoms last more than 7 days or clear up and occur again within a few days.

Keep out of reach of children.

Directions

- Apply as needed.

Inactive Ingredients

Water, Propylene Glycol, Glycerin, Dimethyl Sulfone, Strontium Chloride Hexahydrate, Dimethicone, Cetyl Alcohol, Glyceryl Stearate, Propanediol, Dipotassium Glycyrrhizate, Polysorbate 20, PEG-40 Stearate, Laureth-4, Porphyridium Cruentum Extract, Arnica Montana Flower Extract, sh-Oligopeptide-1 (EGF), sh-Oligopeptide-2 (IGF-1), sh-Polypeptide-1 (bFGF), sh-Polypeptide-9 (VEGF), sh-Polypeptide-11 (FGF-1), Bacillus/Folic Acid Ferment Filtrate Extract, Octyldodecyl Xyloside, Butylene Glycol, Sodium Hyaluronate, 1,2-Hexanediol, Acetyl Glutamine, Octyldodecanol, PEG-30 Dipolyhydroxystearate, Sorbitan Tristearate, Lecithin, Phenoxyethanol, Benzyl Alcohol, Caprylyl Glycol, Potassium Sorbate, Disodium EDTA, Sodium Benzoate.

Multi-Vit Sun Protector SPF 30

Drug Facts

ACTIVE INGREDIENT

Active Ingredient | Purpose
Titanium Dioxide 9% | Sunscreen
Octocrylene 4.8% | Sunscreen
Butyl Methoxydibenzoylmethane 1.44% | Sunscreen

Uses

- Help prevent sunburn.

Warnings

For external use only.

Do not use

- on damage or broken skin.

When using this product

- keep out of eyes. Rinse with water to remove.

Stop use and ask a doctor

- if rash or irritation develops and lasts.

Keep out of reach of children.

- If product is swallowed, get medical help or contact a poison control center right away.

Directions

- Apply liberally 15 minutes before sun exposure and as needed.
- Use a water-resistant sunscreen if swimming or sweating.
- Reapply at least every 2 hours.
- Children under 6 months: Ask a doctor.
- Sun Protection Measures.
  Spending time in the sun increases your risk of skin cancer and early skin aging. To decrease this risk, regularly use a sunscreen with a broad- spectrum SPF value of 15 or higher and other sun protection measures including:
- limit time in the sun, especially from 10 a.m.-2 p.m.
- wear long-sleeved shirts, pants, hats, and sunglasses.

Other Information

- Sun alert: Limiting sun exposure, wearing protective clothing, and using sunscreens may reduce the risks of skin aging, skin cancer, and other harmful effects of the sun.
- Protect this product from excessive heat and direct sun.

Inactive Ingredients

Water, Isononyl Isononanoate, Cyclopentasiloxane, Isohexadecane, Glyceryl Stearate, PEG 100 Stearate, Glycerin, Silica, Potassium Cetyl Phosphate, Sorbitol, Sorbitan Stearate, Magnesium Aluminum Silicate, Xanthan Gum, Sodium Phytate, Xylitol, Nicotinamide, Butyrospermum Parkii (Shea) Butter, Tocopheryl Acetate, Ascorbyl Tetraisopalmitate, Ectoin, Phenoxyethanol, Anhydroxylitol, Stearic Acid, Alumina, PPG-3 Benzyl Ether Myristate, PVP, Xylitylglucoside, Citrus Aurantium Bergamia fruit oil, Fragrance, Sodium Polyacrylate, Ethylhexyl Cocoate, Caprylyl Glycol, Alcohol.

Developed + Dist by NOON Aesthetics
TLV, 62153

PRINCIPAL DISPLAY PANEL - Kit Carton

AESTHETICS

Post-Procedure Treatment Program

MicroSoft Cleanser 15 mL / 0.5 Fl. Oz.
Smart Occlusion System 15 mL / 0.5 Fl. Oz.
Halo-Ronic Serum 15 mL / 0.5 Fl. Oz.

Optimal Moisturizing Guardian 15 mL / 0.5 Fl. Oz.
DeFlame 15 mL / 0.5 Fl. Oz.
Multi-Vit Sun Protector SPF 30 15 mL / 0.5 Fl. Oz.